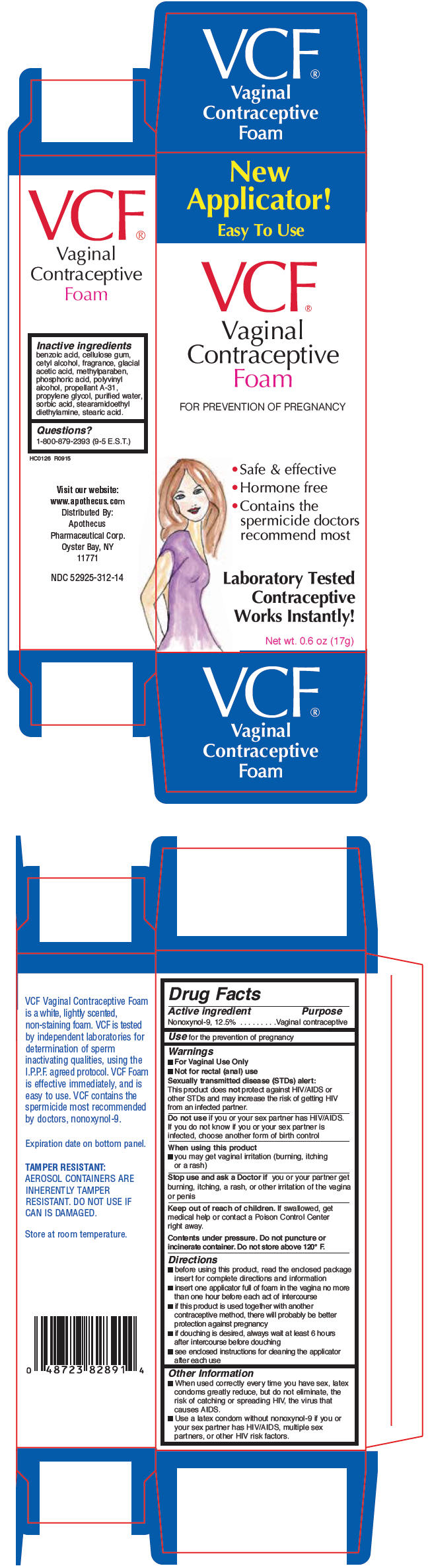 DRUG LABEL: VCF CONTRACEPTIVE
NDC: 52925-312 | Form: AEROSOL, FOAM
Manufacturer: APOTHECUS PHARMACEUTICAL CORP
Category: otc | Type: HUMAN OTC DRUG LABEL
Date: 20181211

ACTIVE INGREDIENTS: NONOXYNOL-9 125 mg/1 g
INACTIVE INGREDIENTS: BENZOIC ACID; CARBOXYMETHYLCELLULOSE SODIUM, UNSPECIFIED FORM; CETYL ALCOHOL; ACETIC ACID; METHYLPARABEN

VCF® VAGINAL CONTRACEPTIVE FOAM

Drug Facts

Active ingredient

Nonoxynol-9, 12.5%

Purpose

Vaginal contraceptive

Use

for the prevention of pregnancy

Warnings

- For Vaginal Use Only
- Not for rectal (anal) use

Sexually transmitted disease (STDs) alert

This product does not protect against HIV/AIDS or other STDs and may increase the risk of getting HIV from an infected partner.

Do not use if you or your sex partner has HIV/AIDS. If you do not know if you or your sex partner is infected, choose another form of birth control

When using this product

- you may get vaginal irritation (burning, itching or a rash)

Stop use and ask a Doctor if you or your partner get burning, itching, a rash, or other irritation of the vagina or penis

Keep out of reach of children. If swallowed, get medical help or contact a Poison Control Center right away.

Contents under pressure. Do not puncture or incinerate container. Do not store above 120° F.

Directions

- before using this product, read the enclosed package insert for complete directions and information
- insert one applicator full of foam in the vagina no more than one hour before each act of intercourse
- if this product is used together with another contraceptive method, there will probably be better protection against pregnancy
- if douching is desired, always wait at least 6 hours after intercourse before douching
- see enclosed instructions for cleaning the applicator after each use

Other Information

- When used correctly every time you have sex, latex condoms greatly reduce, but do not eliminate, the risk of catching or spreading HIV, the virus that causes AIDS.
- Use a latex condom without nonoxynol-9 if you or your sex partner has HIV/AIDS, multiple sex partners, or other HIV risk factors.

Inactive ingredients

benzoic acid, cellulose gum, cetyl alcohol, fragrance, glacial acetic acid, methylparaben, phosphoric acid, polyvinyl alcohol, propellant A-31, propylene glycol, purified water, sorbic acid, stearamidoethyl diethylamine, stearic acid.

Questions?

1-800-879-2393 (9-5 E.S.T.)

Distributed By:
Apothecus
Pharmaceutical Corp.
Oyster Bay, NY
11771

PRINCIPAL DISPLAY PANEL - 17 g Can Box

New
Applicator!

Easy To Use

VCF®

Vaginal
Contraceptive
Foam

FOR PREVENTION OF PREGNANCY

- Safe & effective
- Hormone free
- Contains the
  spermicide doctors
  recommend most

Laboratory Tested
Contraceptive
Works Instantly!

Net wt. 0.6 oz (17g)